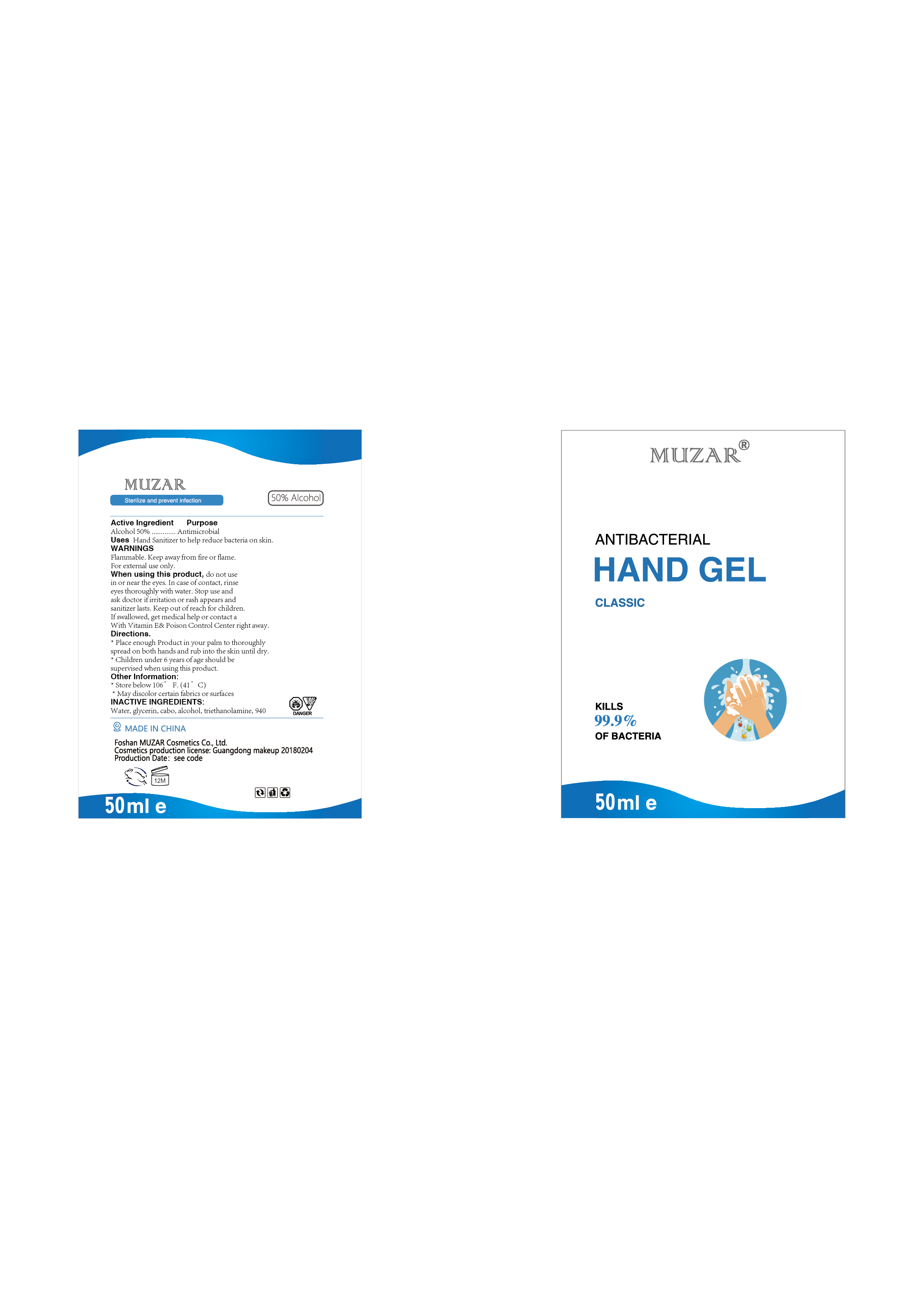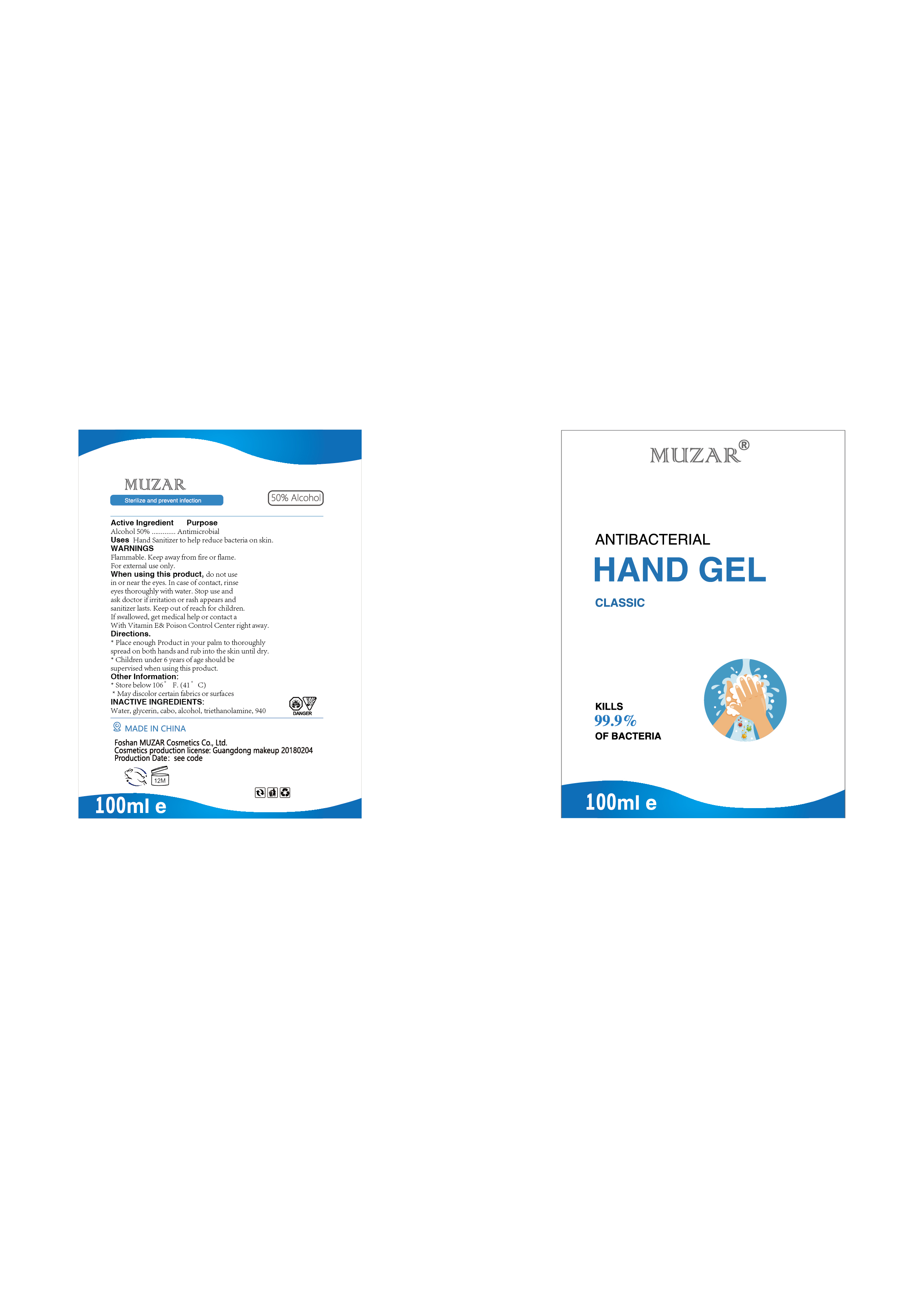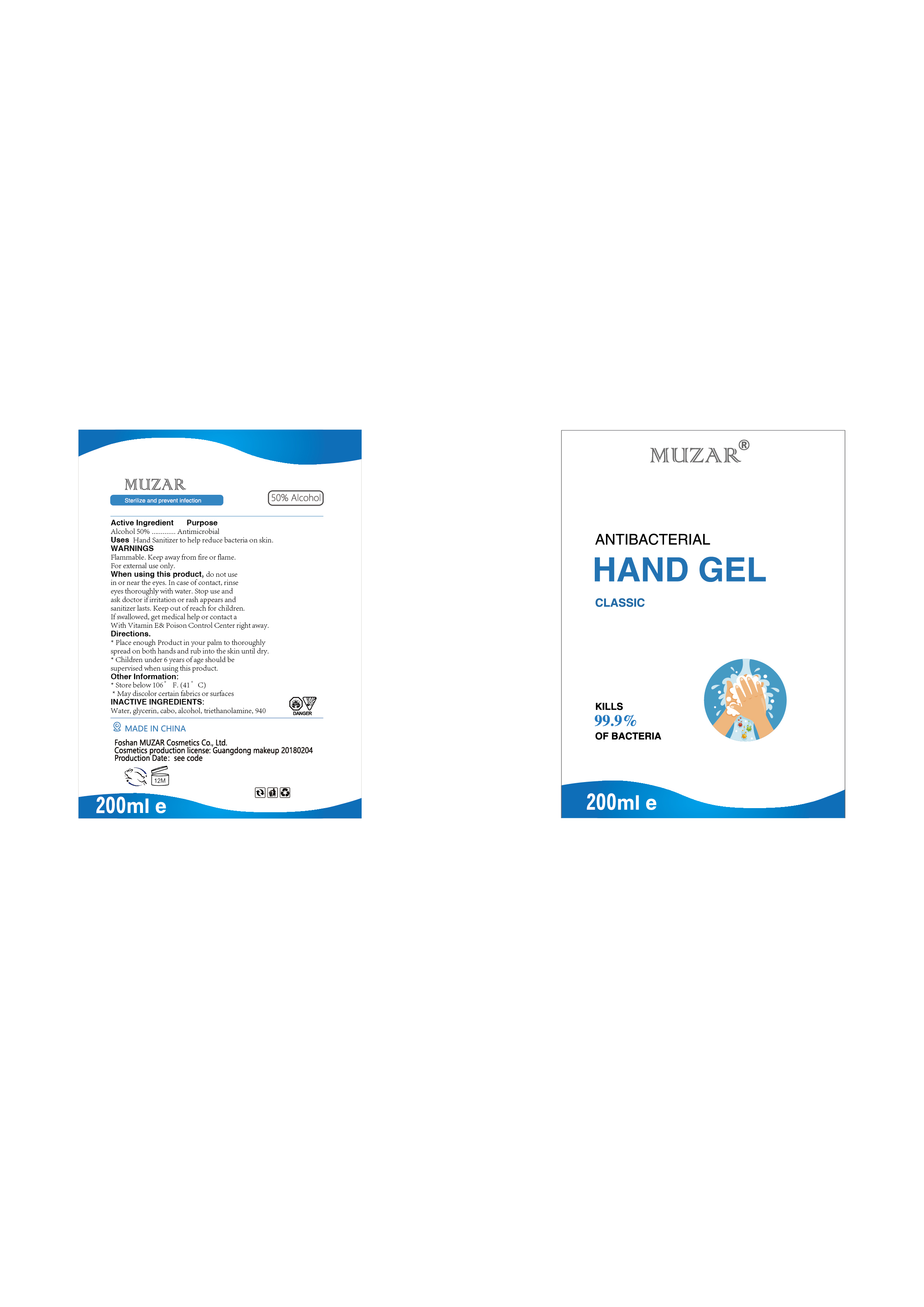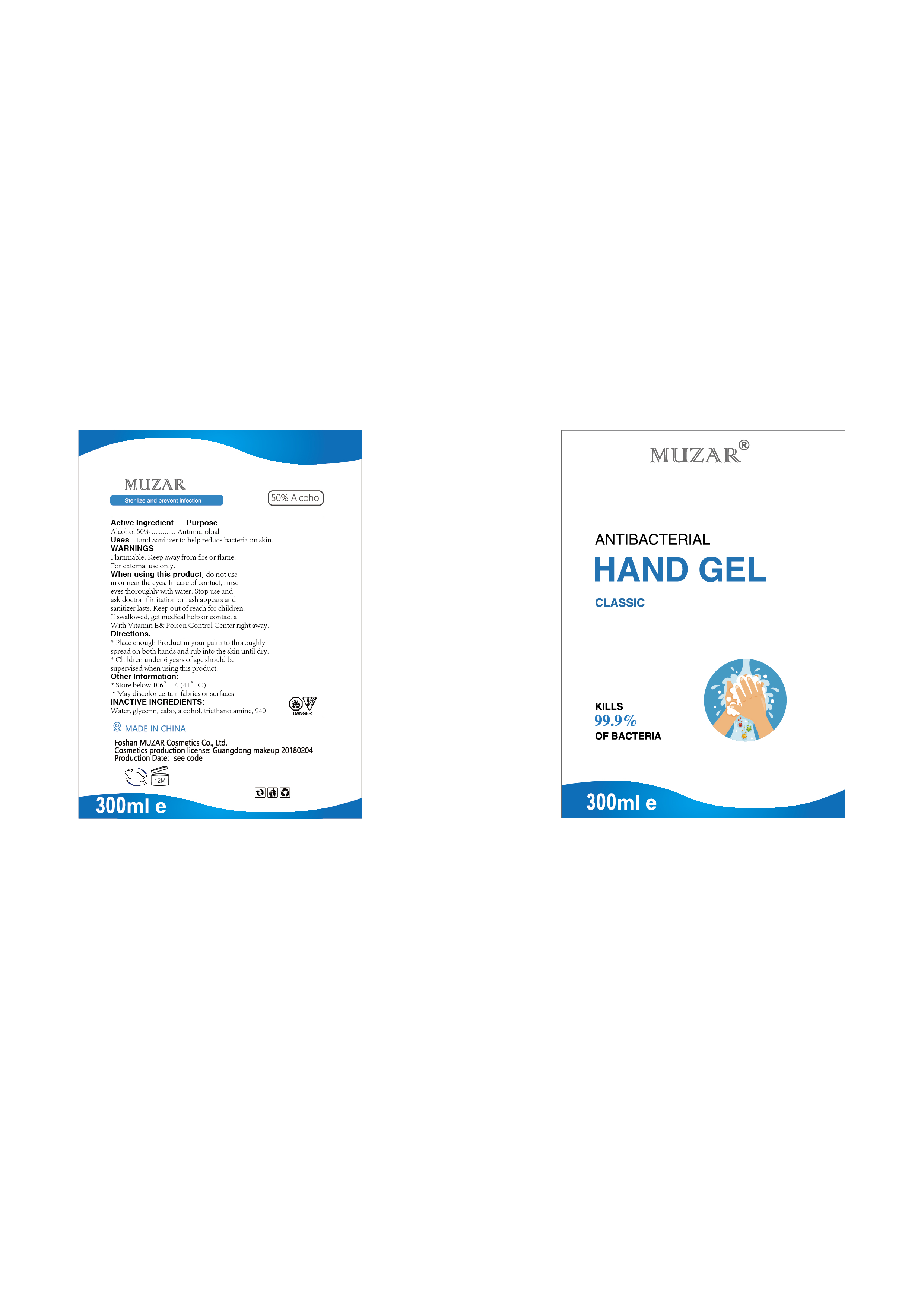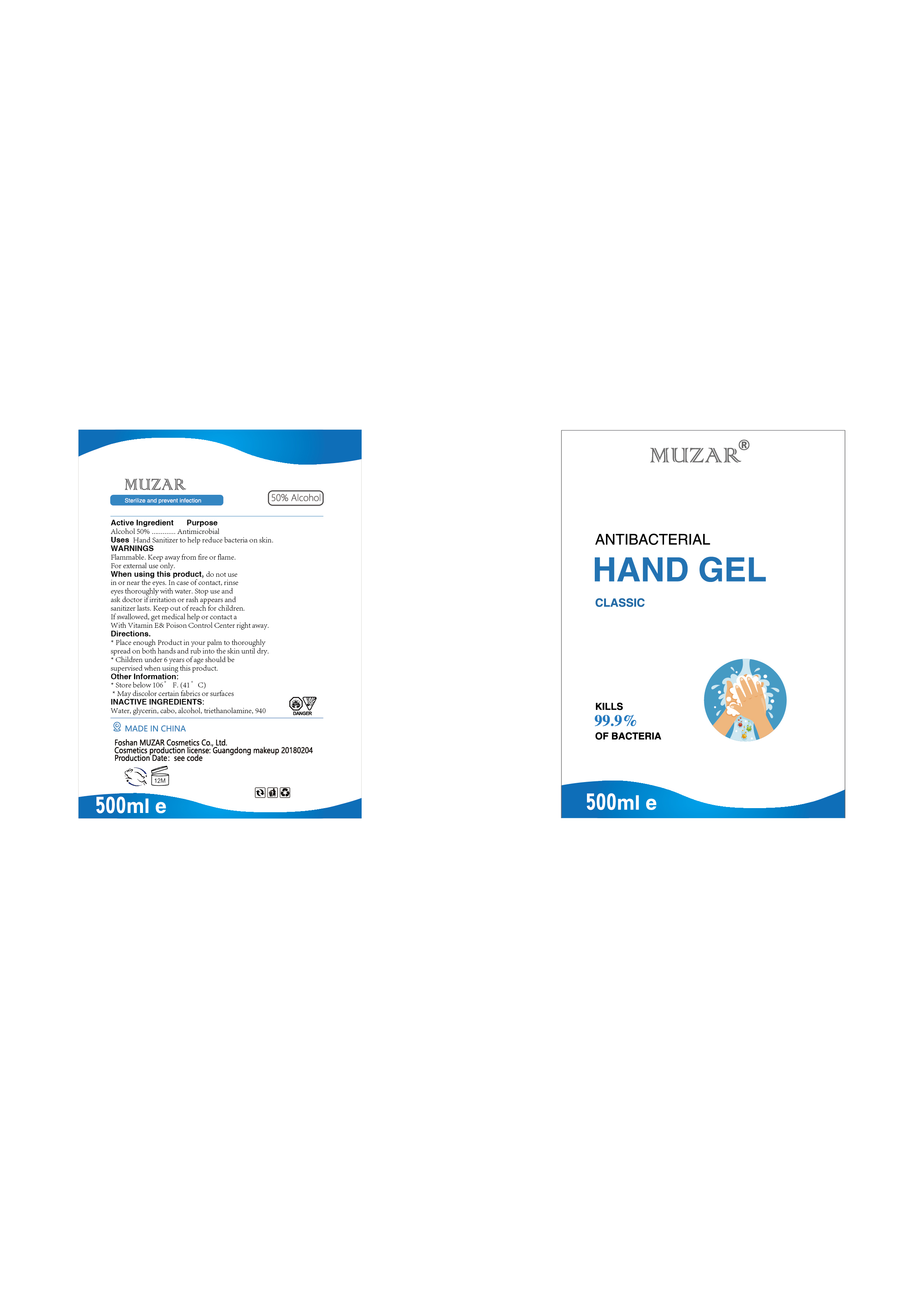 DRUG LABEL: Antibacterial Hand gel
NDC: 74041-001 | Form: GEL
Manufacturer: Foshan MUZAR Cosmetics Co., Ltd
Category: otc | Type: HUMAN OTC DRUG LABEL
Date: 20200331

ACTIVE INGREDIENTS: ALCOHOL 50 mL/100 mL
INACTIVE INGREDIENTS: WATER; GLYCERIN; TROLAMINE

Active Ingredient

Alcohol 50%

Purpose

Antimicrobial

Uses

Hand Sanitizer to help reduce bacteria on skin.

Warnings

Flammable. Keep away from fire or flame.For external use only.

When using this product

do not use in or near the eyes.In case of contact,rinse eyes thoroughly with water.Stop use and ask doctor if irritation or rash appears and lasts.Keep out of reach for children. if swallowed,get medical help or contact a With Vitamin E& Poison Control Center right away.

Directions

Place enough Product in your palm to thoroughly spread on both hands and rub into the skin until dry.

Children under 6 years of age should be supervised when using this product.

Other information

Store below 106° F.(41 ° C)

May discolor certain fabrics or surfaces

Inactive ingredients

Water,glycerin,cabo,alcohol,triethanolamine,940